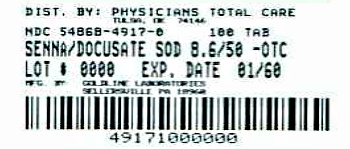 DRUG LABEL: Senna/Docusate Sodium
NDC: 54868-4917 | Form: TABLET, FILM COATED
Manufacturer: Physicians Total Care, Inc.
Category: otc | Type: HUMAN OTC DRUG LABEL
Date: 20120420

ACTIVE INGREDIENTS: Docusate sodium 50 mg/1 1; Sennosides 8.6 mg/1 1
INACTIVE INGREDIENTS: carnauba wax; silicon dioxide; croscarmellose sodium; dibasic calcium phosphate dihydrate; D&C yellow NO. 10; FD&C yellow NO. 6; hypromelloses; magnesium stearate; cellulose, microcrystalline; polyethylene glycol; sodium benzoate; stearic acid; starch, tapioca; tartaric acid; titanium dioxide; aluminum oxide

Senna-S

TAMPER-EVIDENT: Do not use this product if imprinted foil seal over the mouth of the bottle is cut, torn, broken or missing.

Drug Facts

Active ingredients (in each tablet) | Purposes
Docusate sodium 50 mg | Stool softener
Sennosides 8.6 mg | Stimulant laxative

 | Purposes
Docusate sodium 50 mg | Stool softener
Sennosides 8.6 mg | Stimulant laxative

Uses

- relieves occasional constipation (irregularity)
- generally causes bowel movement in 6 to 12 hours

Warnings

Do not use

- this product if you are presently taking mineral oil, unless directed by a doctor
- laxative products for longer than 1 week unless directed by a doctor

Ask a doctor before use if you have

- stomach pain
- nausea
- vomiting
- a sudden change in bowel habits that persists over 2 weeks

Stop use and ask a doctor if you

- have rectal bleeding
- fail to have a bowel movement after use of a laxative

these could be signs of a serious condition

PREGNANCY OR BREAST FEEDING

If pregnant or breast-feeding, ask a health professional before use.

Keep out of reach of children. In case of overodse, get medical help or contact a Poison Control Center right away.

Directions

- take preferably at bedtime or as directed by a doctor
- if you do not have a comfortable bowel movement by the second day, increase dose by one tablet (do not exceed maximum dosage) or decrease dose until you are comfortable

age | starting dosage | maximum dosage
adults and children 12 years and older | 2 tablets once a day | 4 tablets twice a day
children 6 to under 12 years | 1 tablet once a day | 2 tablets twice a day
children 2 to under 6 years | 1/2 tablet once a day | 1 tablet twice a day
children under 2 years | ask a doctor | ask a doctor

Other information

- each tablet contains: calcium 20 mg, sodium 6 mg (LOW SODIUM)
- store at room temperature 15° to 30°C (59° to 86°F)

Inactive ingredients

carnauba wax, colloidal silicon dioxide, croscarmellose sodium, dibasic calcium phosphate dihydrate, D&C yellow #10 aluminum lake, FD&C yellow #6 aluminum lake, hypromellose, magnesium stearate, microcrystalline cellulose, polyethylene glycol, sodium benzoate, stearic acid, tapioca starch [may contain these ingredients] , tartaric acid, titanium dioxide

Questions?

call 1-888-838-2872, weekdays, 8 AM-5 PM Eastern Time

†This product is not manufactured or distributed by Purdue Products L.P., owner of the registered trademark Senokot-S®

Distributed by: GOLDLINE LABORATORIES, INC.
Sellersville, PA 18960 Dist. 1999 0110REV 89

Additional barcode labeling by:
Physicians Total Care, Inc.
Tulsa, Oklahoma 74146

PRINCIPAL DISPLAY PANEL - 100 Tablet Bottle

NDC 54868-4917-0

TAMPER-EVIDENT

Senna/Docusate Sodium Tablets
(brand of standardized senna concentrate
equivalent to 8.6 mg sennosides
and docusate sodium 50 mg)

Natural Vegetable Stimulant
Laxative And Stool Softener

100 TABLETS

Compare to active ingredients
of Senokot-S® Tablets†